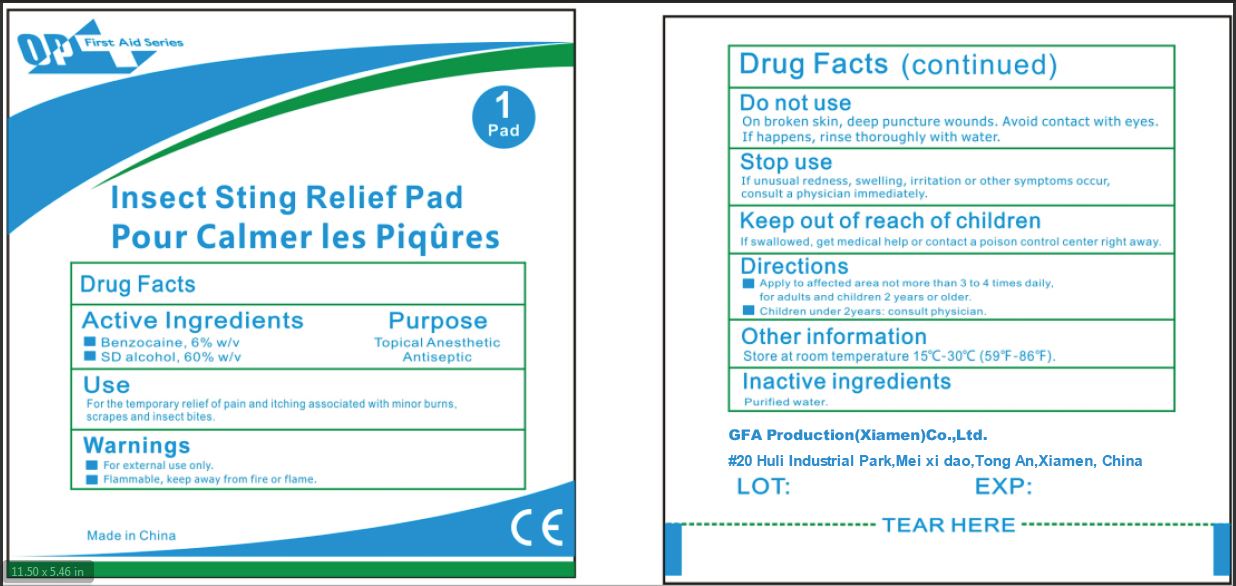 DRUG LABEL: Insect Sting Relief
NDC: 50814-040 | Form: CLOTH
Manufacturer: GFA Production (Xiamen) Co., Ltd.
Category: otc | Type: HUMAN OTC DRUG LABEL
Date: 20250430

ACTIVE INGREDIENTS: BENZOCAINE 60 mg/1 mL; ALCOHOL 600 mg/1 mL
INACTIVE INGREDIENTS: WATER

Insect Sting Relief Pad

Active Ingredients

- Benzocaine, 6% w/v
- SD alcohol, 60% w/v

Purpose

Topical Anesthetic

Antiseptic

Use

- For the temporary relief of pain and itching associated with minor burns, scrapes and insect bites.

Warnings

- For external use only.
- Flammable, keep away from fire or flame.

Do not use

On broken skin, deep puncture wounds. Avoid contact with eyes. If happens, rinse thoroughly with water.

Stop use

If unsual redness, swelling, irritation or other symptoms occur, consult a physician immediately.

Keep out of reach of children

If swallowed, get medical help or contact a poison control center right away.

Directions

- Apply to affected area nor more than 3 to 4 times daily.
- Children under 2 years: consult physician.

Other information

Store at room temperature 15°C-30°C (59°F-86°F)

Inactive ingredients

Purified water.